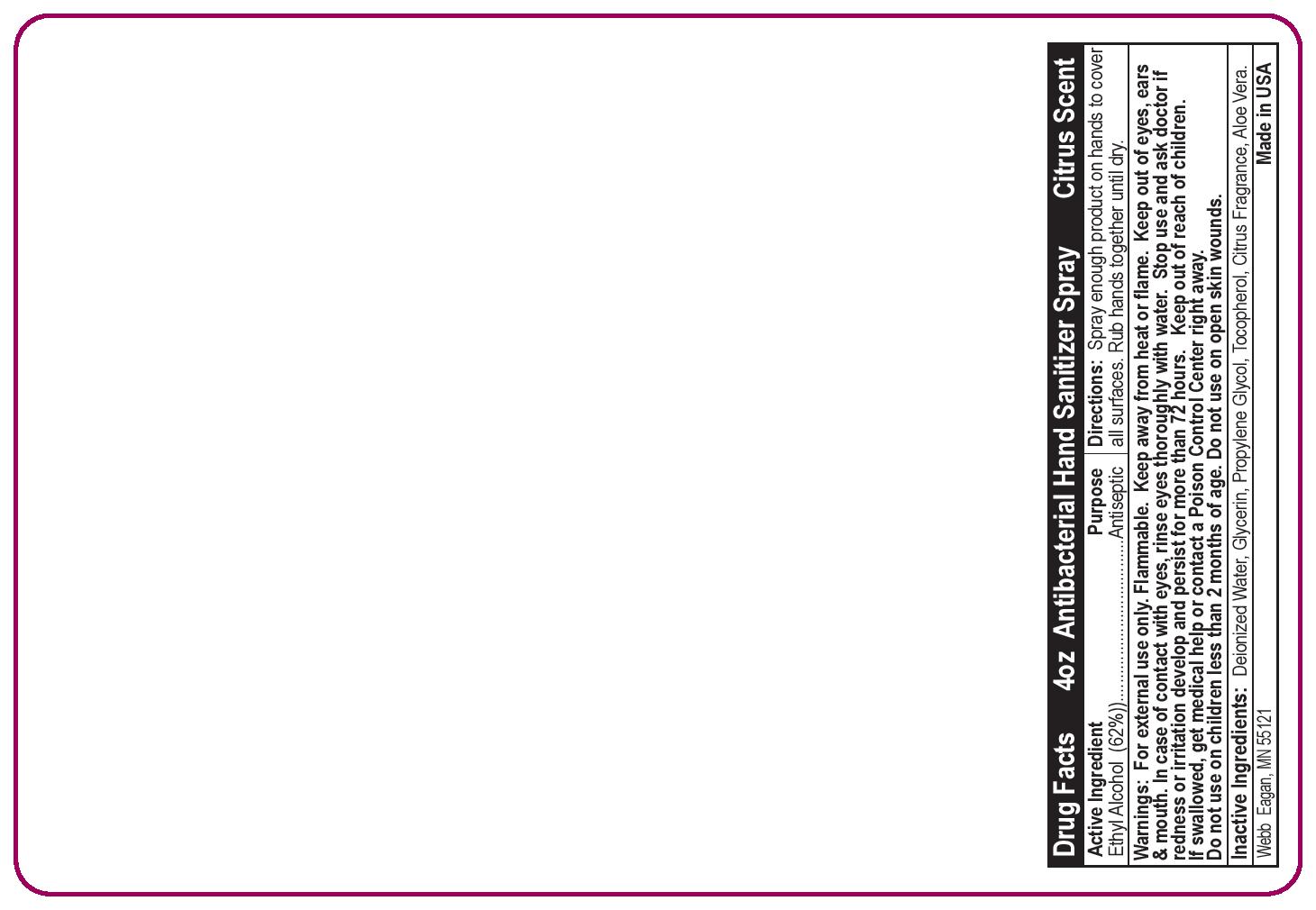 DRUG LABEL: Alcohol Hand Sanitizer
NDC: 70445-412 | Form: SPRAY
Manufacturer: Webb Business Promotion
Category: otc | Type: HUMAN OTC DRUG LABEL
Date: 20220104

ACTIVE INGREDIENTS: ALCOHOL 62 mL/100 mL
INACTIVE INGREDIENTS: TOCOPHEROL; ALOE VERA LEAF; GLYCERIN; WATER; PROPYLENE GLYCOL

Antibacterial Hand Sanitizer

Directions:

Spray enough product on hands to cover all surfaces. Rub hands together until dry.

Active Ingridient

Ethyl Alcohol (62%).

Inactive Ingredients:

Deionized Water, Glycerin, Propylene Glycol, Tocopherol, Citrus Fragrance, Aloe Vera.

Keep out of reach of children.

Do not use on children less than 2 months of age. Do not use on open skin wounds.

WARNINGS

For external use only. Flammable. Keep away from heat or flame. Keep out of eyes, eras & mouth. In case of contact with eyes, rinse eyes thoroughly with water. If swallowed, get medical help or contact a Poison Control Center right away.

INDICATIONS AND USAGE

Antibacterial hand sanitizer spray.

PURPOSE

Antiseptic.